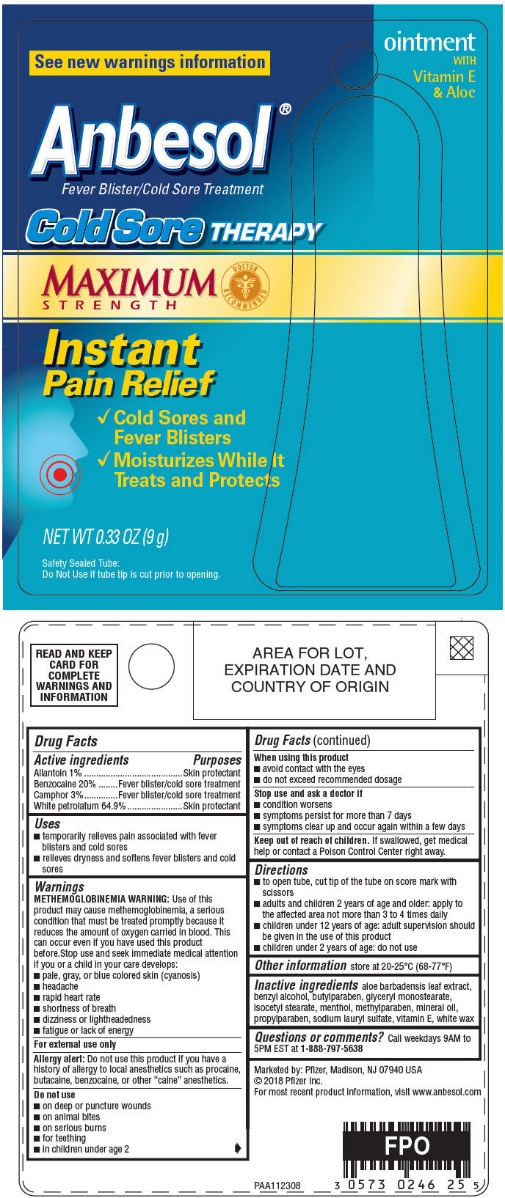 DRUG LABEL: ANBESOL COLD SORE THERAPY
NDC: 0573-0246 | Form: OINTMENT
Manufacturer: GlaxoSmithKline Consumer Healthcare Holdings (US) LLC
Category: otc | Type: HUMAN OTC DRUG LABEL
Date: 20201125

ACTIVE INGREDIENTS: ALLANTOIN 10 mg/1 g; BENZOCAINE 200 mg/1 g; CAMPHOR (SYNTHETIC) 30 mg/1 g; PETROLATUM 649 mg/1 g
INACTIVE INGREDIENTS: ALOE VERA LEAF; .ALPHA.-TOCOPHEROL; BENZYL ALCOHOL; BUTYLPARABEN; GLYCERYL MONOSTEARATE; ISOCETYL STEARATE; MENTHOL, UNSPECIFIED FORM; METHYLPARABEN; MINERAL OIL; PROPYLPARABEN; SODIUM LAURYL SULFATE; WHITE WAX

Drug Facts

Active Ingredients

Allantoin 1%

Benzocaine 20%

Camphor 3%

White petrolatum 64.9%

Purposes

Skin protectant

Fever blister/cold sore treatment

Fever blister/cold sore treatment

Skin protectant

Uses

1. temporarily relieves pain associated with fever blisters and cold sores
2. relieves dryness and softens fever blisters and cold sores

Warnings

METHEMOGLOBINEMIA WARNING

Use of this product may cause methemoglobinemia, a serious condition that must be treated promptly because it reduces the amount of oxygen carried in blood. This can occur even if you have used this product before. Stop use and seek immediate medical attention if you or a child in your care develops:

1. pale, gray, or blue colored skin (cyanosis)
2. headache
3. rapid heart rate
4. shortness of breath
5. dizziness or lightheadedness
6. fatigue or lack of energy

For external use only

Allergy alert

Do not use this product if you have a history of allergy to local anesthetics such as procaine, butacaine, benzocaine, or other "caine" anesthetics.

Do not use

1. on deep or puncture wounds
2. on animal bites
3. on serious burns
4. for teething
5. in children under age 2

When using this product

1. avoid contact with the eyes
2. do not exceed recommended dosage

Stop use and ask a doctor if

1. condition worsens
2. symptoms persist for more than 7 days
3. symptoms clear up and occur again within a few days

Keep out of reach of children. If swallowed, get medical help or contact a Poison Control Center right away.

Directions

1. to open tube, cut tip of the tube on score mark with scissors
2. adults and children 2 years of age and older: apply to the affected area not more than 3 to 4 times daily
3. children under 12 years of age: adult supervision should be given in the use of this product
4. children under 2 years of age: do not use

Other information

store at 20-25°C (68-77°F)

Inactive ingredients

aloe barbadensis leaf extract, benzyl alcohol, butylparaben, glyceryl monostearate, isocetyl stearate, menthol, methylparaben, mineral oil, propylparaben, sodium lauryl sulfate, vitamin E, white wax

Questions or comments?

Call weekdays 9AM to 5PM EST at 1-888-797-5638

PRINCIPAL DISPLAY PANEL - 9 g Tube Blister Pack Label

ointment
WITH
Vitamin E
& Aloe

See new warnings information

Anbesol®
Fever Blister/Cold Sore Treatment

Cold Sore THERAPY

MAXIMUM
STRENGTH

DOCTOR
RECOMMENDED

Instant
Pain Relief

1. Cold Sores and
  Fever Blisters
2. Moisturizes While It
  Treats and Protects

NET WT 0.33 OZ (9 g)

Safety Sealed Tube:
Do Not Use if tube tip is cut prior to opening.